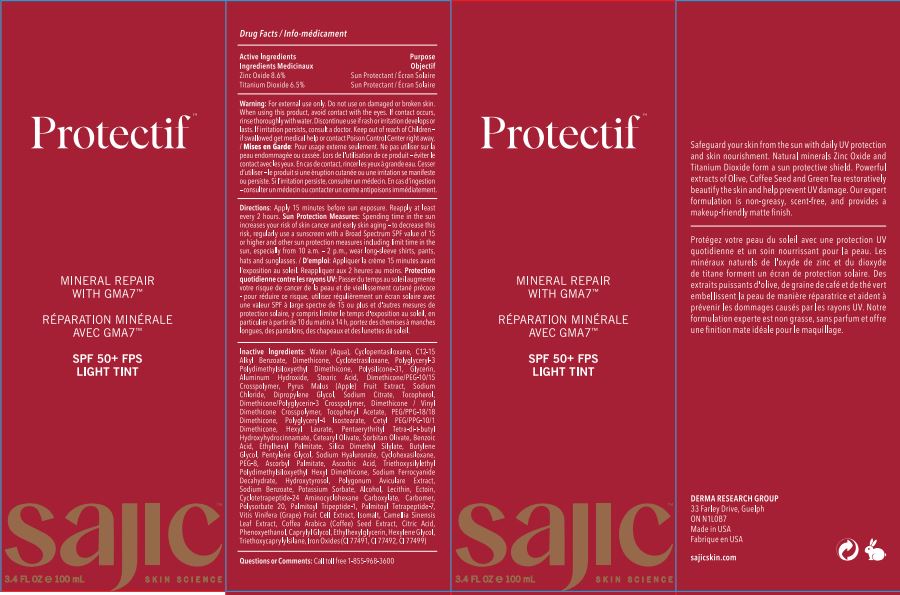 DRUG LABEL: Protectif fair tint
NDC: 82038-003 | Form: CREAM
Manufacturer: Derma Research Group Inc.
Category: otc | Type: HUMAN OTC DRUG LABEL
Date: 20220627

ACTIVE INGREDIENTS: ZINC OXIDE 8.6 g/100 g; TITANIUM DIOXIDE 6.5 g/100 g
INACTIVE INGREDIENTS: PALMITOYL TRIPEPTIDE-1; PALMITOYL TETRAPEPTIDE-7; SILICA DIMETHYL SILYLATE; POLYGONUM AVICULARE TOP; FERRIC OXIDE RED; VITIS VINIFERA STEM; ARABICA COFFEE BEAN; CITRIC ACID MONOHYDRATE; PHENOXYETHANOL; PENTYLENE GLYCOL; POLYSORBATE 20; DIMETHICONE/VINYL DIMETHICONE CROSSPOLYMER (SOFT PARTICLE); DIMETHICONE/PEG-10/15 CROSSPOLYMER; SODIUM CHLORIDE; ASCORBYL PALMITATE; SODIUM FERROCYANIDE DECAHYDRATE; HYDROXYTYROSOL; CARBOMER HOMOPOLYMER, UNSPECIFIED TYPE; CETYL PEG/PPG-10/1 DIMETHICONE (HLB 4); SORBITAN OLIVATE; WATER; CYCLOMETHICONE 5; CYCLOMETHICONE 4; DIMETHICONE; POLYGLYCERYL-3 POLYDIMETHYLSILOXYETHYL DIMETHICONE (4000 MPA.S); ALUMINUM HYDROXIDE; STEARIC ACID; DIPROPYLENE GLYCOL; SODIUM CITRATE; PEG/PPG-18/18 DIMETHICONE; ALKYL (C12-15) BENZOATE; VINYL DIMETHICONE/METHICONE SILSESQUIOXANE CROSSPOLYMER; ISOMALT; HEXYL LAURATE; TOCOPHEROL; .ALPHA.-TOCOPHEROL ACETATE; POLYGLYCERYL-4 ISOSTEARATE; HYALURONATE SODIUM; POLYETHYLENE GLYCOL 400; TRIETHOXYSILYLETHYL POLYDIMETHYLSILOXYETHYL HEXYL DIMETHICONE; ALCOHOL; GLYCERIN; SODIUM BENZOATE; POTASSIUM SORBATE; CAPRYLYL GLYCOL; ETHYLHEXYLGLYCERIN; ASCORBIC ACID; LECITHIN, SOYBEAN; CYCLOTETRAPEPTIDE-24 AMINOCYCLOHEXANE CARBOXYLATE; GREEN TEA LEAF; DIMETHICONE/POLYGLYCERIN-3 CROSSPOLYMER; BENZOIC ACID; ETHYLHEXYL PALMITATE; BUTYLENE GLYCOL; CYCLOMETHICONE 6; ECTOINE; HEXYLENE GLYCOL; TRIETHOXYCAPRYLYLSILANE; FERROSOFERRIC OXIDE; CETEARYL OLIVATE; APPLE; PENTAERYTHRITOL TETRAKIS(3-(3,5-DI-TERT-BUTYL-4-HYDROXYPHENYL)PROPIONATE); FERRIC OXIDE YELLOW

Drug Facts

Active Ingredients

Zinc Oxide 8.6 %

Titanium Dioxide 6.5 %

Purpose

Sun Protectant

Uses

Helps Prevent sunburn

Warning

For external use only

Do not use

Do not use on damaged or broken skin.

When using

When using this product, avoid contect with eyes.If contect occurs, rinse throughly with water

stop use

Discontinue use if rash or irritation develops or lasts. If irritation persists,consultant a doctor

Keep out of reach of children

If swallowed get medical help or contect poison control center right away.

DOSAGE AND ADMINISTRATION

Directions: Apply 15 minutes before sun exposure. Reapply at least every 2 hours. Sun Protection Measures: Spending time in the sun increases your risk of skin cancer and early skin aging - to decrease this risk, regularly use a sunscreen with a Broad Spectrum SPF value of 15 or higher and other sun protection measures including limit time in the sun, especially from 10 a.m. - 2 p.m., wear long-sleeve shirts, pants, hats and sunglasses.

OTHER SAFETY INFORMATION

NA

Inactive Ingredients:

Water (Aqua), Cyclopentasiloxane,C12-15 Alkyl Benzoate,Dimethicone,Cyclotetrasiloxane,Polyglyceryl-3 Polydimethylsiloxyethyl Dimethicone, Polysilicone-31,Glycerin,Aluminum Hydroxide,Stearic Acid,Dimethicone/PEG-10/15 Crosspolymer,

Pyrus Malus (Apple) Fruit Extract,Sodium Chloride,Dipropylene Glycol,Sodium Citrate,Tocopherol,Dimethicone/Polyglycerin-3 Crosspolymer,Dimethicone / Vinyl Dimethicone Crosspolymer,Tocopheryl Acetate,PEG/PPG-18/18 Dimethicone,

Polyglyceryl-4 Isostearate,Cetyl PEG/PPG-10/1 Dimethicone,Hexyl Laurate,Pentaerythrityl Tetra-di-t-butyl Hydroxyhydrocinna mate, Cetearyl Olivate,Sorbitan Olivate, Benzoic Acid,Ethylhexyl Palmitate,Silica Dimethyl Silylate, Butylene Glycol,

Pentylene Glycol,Sodium Hyaluronate, Cyclohexasiloxane,PEG-8, Ascorbyl Palmitate, Ascorbic Acid,Triethoxysilylethyl Polydimethylsiloxyethyl Hexyl Dimethicone,Sodium Ferrocyanide Decahydrate,Hydroxytyrosol, Polygonum Aviculare Extract,

Sodium Benzoate, Potassium Sorbate,Alcohol,Lecithin,Ectoin,Cyclotetrapeptide-24 Aminocyclohexane Carboxylate,Carbomer,

Polysorbate 20,Palmitoyl Tripeptide-1, Palmitoyl Tetrapeptide-7,Vitis Vinifera (Grape) Fruit Cell Extract, Isomalt,

Camellia Sinensis Leaf Extract,Coffea Arabica (Coffee) Seed Extract, Citric Acid,Phenoxyethanol,Caprylyl Glycol,Ethylhexylglycerin,

Hexylene Glycol,Triethoxycaprylylsilane, Iron Oxides (CI 77491, CI 77492, CI 77499)